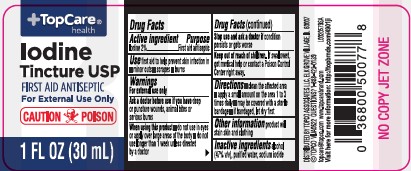 DRUG LABEL: Iodine Tincture
NDC: 76162-088 | Form: SOLUTION/ DROPS
Manufacturer: Topco Associates LLC
Category: otc | Type: HUMAN OTC DRUG LABEL
Date: 20260213

ACTIVE INGREDIENTS: IODINE 20 mg/1 mL
INACTIVE INGREDIENTS: ALCOHOL; WATER; SODIUM IODIDE

Top Care 088.000/098AA
Iodine Tincture USP

Active ingredient

Iodine 2%

Purpose

First aid antiseptic

Use

first aid to help prevent skin infection in

- minor cuts
- scrapes
- burns

Warnings

For external use only

Ask a doctor before use if you have

deep or puncture wounds, animal bites or serious burns

When using this product

- do not use in eyes or apply over large areas of the body
- do not use longer than 1 week unless directed by a doctor

Stop use and ask a doctor

if condition persists or gets worse

Keep out of reach of children.

If swallowed, get medical help or contact a Poison Control Canter right away.

Directions

- clean the affected area
- apply a small amount on the area 1 to 3 times daily
- may be covered with a sterile bandage
- if bandaged, let dry first

Other Information

product will stain skin and clothing

Inactive ingredients

alcohol (47%v/v), purified water, sodium iodide

ADVERSE REACTION

DISTRIBUTED BY TOPCO ASSOCIATES LLC, ELK GROVE VILLAGE, IL 60007

TOPCO VIJA0622 QUESTIONS? 1-888-423-0139

topcare@topco.com www.topcarebrand.com

Visit here for more information: http://topbrnds.com/4901ji

principal display panel

TopCare®

health

Iodine Tincture USP

FIRST AID ANTISEPTIC

For External Use Only

CAUTION POISON

1 FL OZ (30 mL)